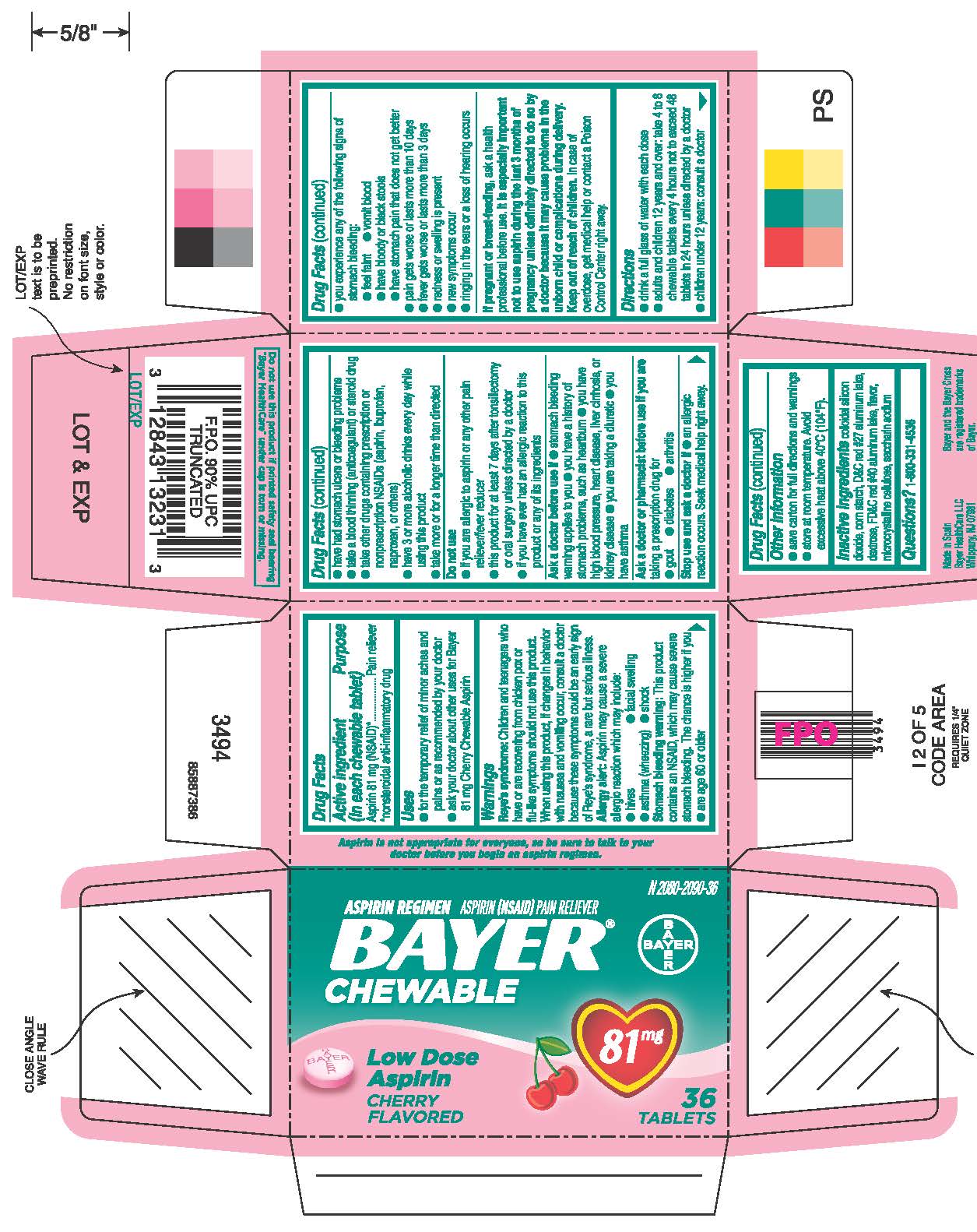 DRUG LABEL: Bayer Chewable - Aspirin Regimen
NDC: 0280-2090 | Form: TABLET, CHEWABLE
Manufacturer: Bayer HealthCare LLC.
Category: otc | Type: HUMAN OTC DRUG LABEL
Date: 20251204

ACTIVE INGREDIENTS: ASPIRIN 81 mg/1 1
INACTIVE INGREDIENTS: SILICON DIOXIDE; STARCH, CORN; ALUMINUM OXIDE; D&C RED NO. 27; DEXTROSE; FD&C RED NO. 40; CELLULOSE, MICROCRYSTALLINE

Bayer Chewable - Aspirin Regimen

Drug Facts

ACTIVE INGREDIENT

Aspirin 81 mg (NSAID) [nonsteroidal anti-inflammatory drug]

Purpose

Pain reliever

Directions

• drink a full glass of water with each dose • adults and children 12 years and over: take 4 to 8 tablets every 4 hours not to exceed 48 tablets in 24 hours unless directed by a doctor • children under 12 years: consult a doctor

Uses

● for the temporary relief of minor aches and pains or as recommended by your

doctor

● ask your doctor about other uses for Bayer 81 mg Cherry Chewable Aspirin

Warnings

Reye’s syndrome: Children and teenagers who have or are recovering from chicken pox or flu-like symptoms should not use this product. When using this product, if changes in behavior with nausea and vomiting occur, consult a doctor because these symptoms could be an early sign of Reye’s syndrome, a rare but serious illness.

Allergy alert: Aspirin may cause a severe allergic reaction which may include:

● hives ● facial swelling ● asthma (wheezing) ● shock

Stomach bleeding warning: This product contains an NSAID, which may cause severe stomach bleeding. The chance is higher if you

● are age 60 or older

● have had stomach ulcers or bleeding problems

● take a blood thinning (anticoagulant) or steroid drug

● take other drugs containing prescription or nonprescription NSAIDs

(aspirin, ibuprofen, naproxen, or others)

● have 3 or more alcoholic drinks every day while using this product

● take more or for a longer time than directed

Do not use

● if you are allergic to aspirin or any other pain reliever/fever reducer

● this product for at least 7 days after tonsillectomy or oral surgery unless

directed by a doctor

● if you have ever had an allergic reaction to this product or any of its

ingredients

Ask a doctor before use if

● stomach bleeding warning applies to you

● you have a history of stomach problems, such as heartburn

● you have high blood pressure, heart disease, liver cirrhosis,

or kidney disease

● you are taking a diuretic

● you have asthma

Ask a doctor or pharmacist before use if you are taking a prescription drug for

● gout ● diabetes ● arthritis

Stop use

● an allergic reaction occurs. Seek medical help right away.

● you experience any of the following signs of stomach bleeding:

● feel faint ● vomit blood ● have bloody or black stools

● have stomach pain that does not get better

● pain gets worse or lasts more than 10 days

● redness or swelling is present

● new symptoms occur

● ringing in the ears or a loss of hearing occurs

If pregnant or breast-feeding, ask a health professional before use . It is especially important not to use aspirin during the last 3 months of pregnancy unless definitely directed to do so by a doctor because it may cause problems in the unborn child or complications during delivery.

Keep out of reach of children. In case of overdose, get medical help or contact a Poison Control Center right away.

Directions

● drink a full glass of water with each dose

● adults and children 12 years and over: take 4 to 8 tablets every 4 hours not to

exceed 48 tablets in 24 hours unless directed by a doctor

● children under 12 years: consult a doctor

Other information

● save carton for full directions and warnings

● store at room temperature

Inactive ingredients

Inactive ingredients colloidal silicon dioxide, corn starch, D&C red #27 aluminum lake, dextrose, FD&C red #40 aluminum lake, flavor, microcrystalline cellulose, saccharin sodium

Questions or comments?1-800-331-4536 (Mon-Fri 9AM – 5PM EST)